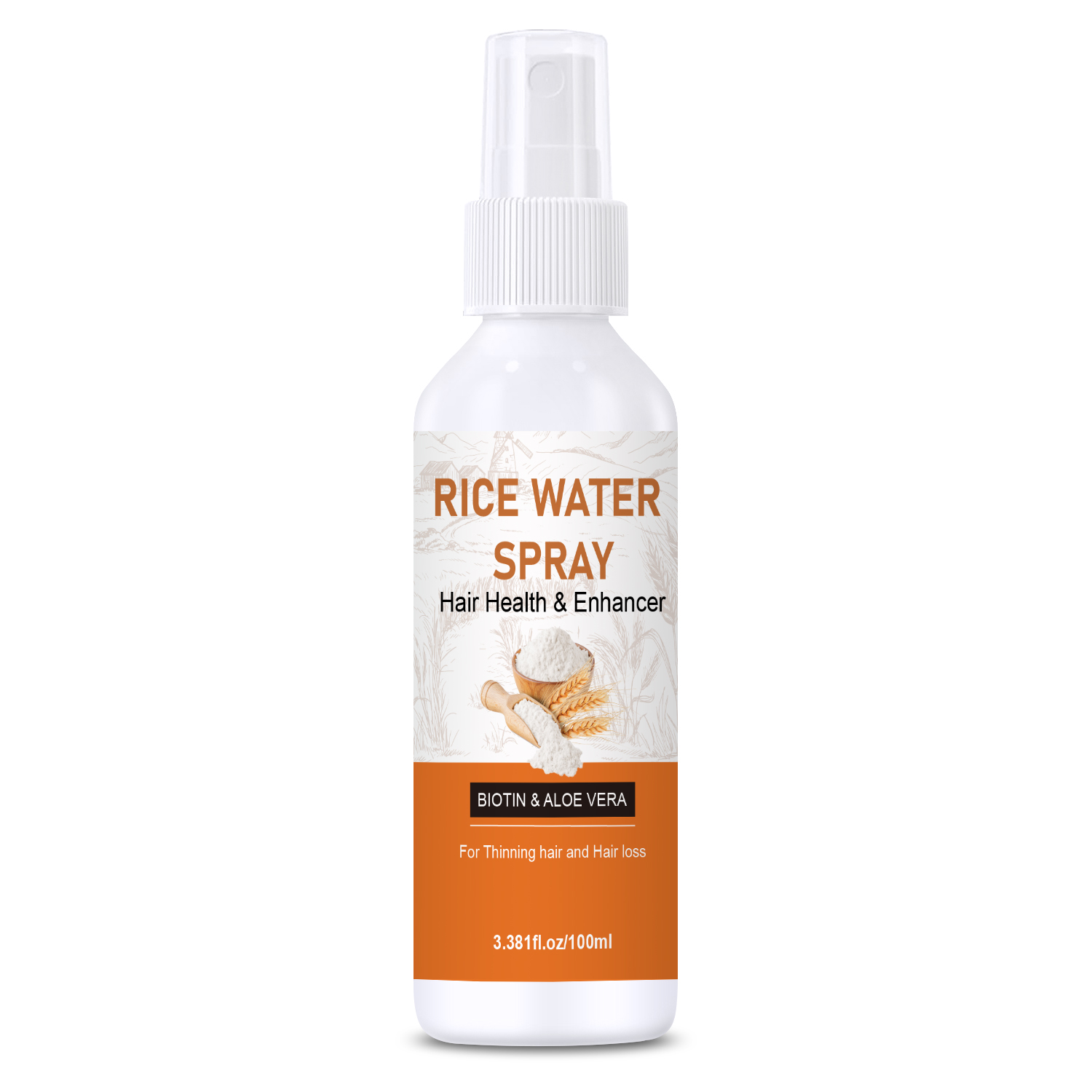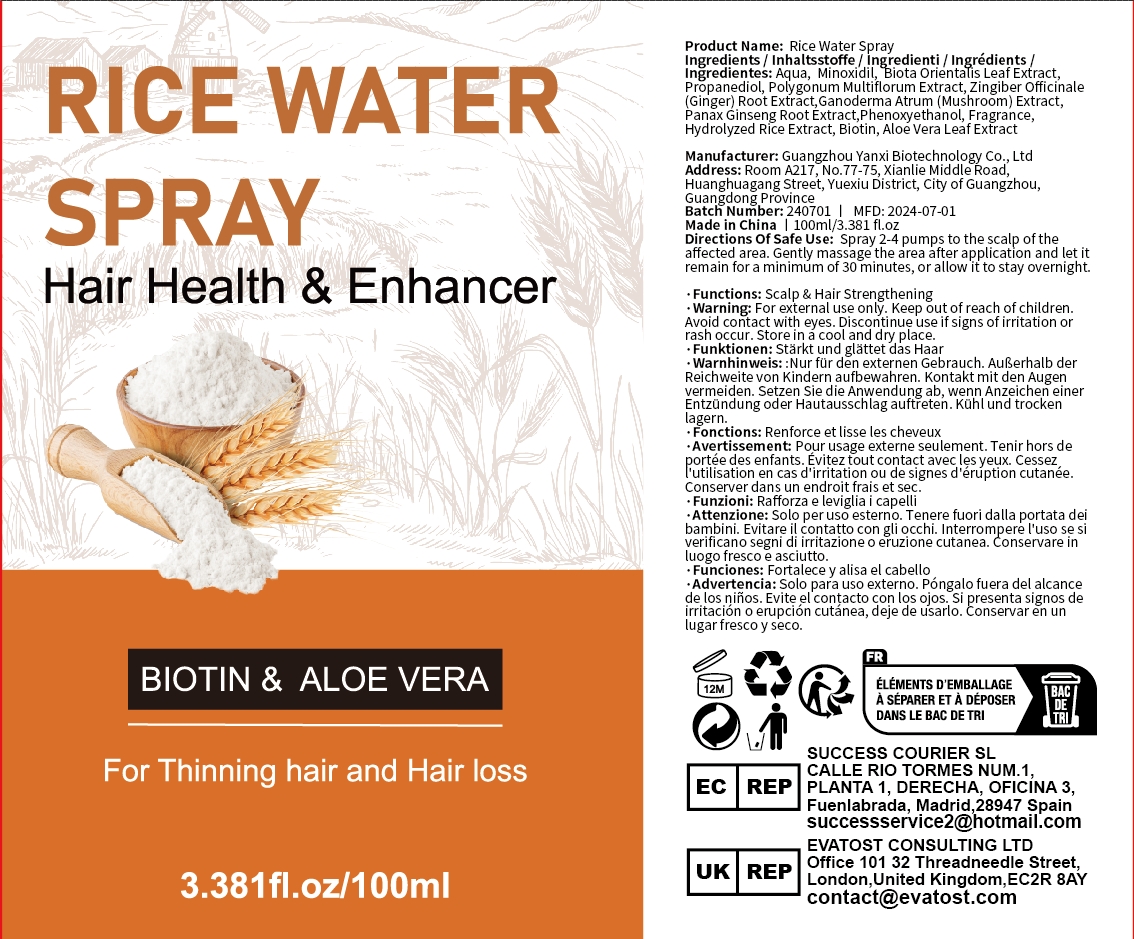 DRUG LABEL: Rice WaterSpray
NDC: 84025-181 | Form: SPRAY
Manufacturer: Guangzhou Yanxi Biotechnology Co.. Ltd
Category: otc | Type: HUMAN OTC DRUG LABEL
Date: 20240904

ACTIVE INGREDIENTS: MINOXIDIL 5 mg/100 mL; PROPANEDIOL 3 mg/100 mL
INACTIVE INGREDIENTS: WATER

DOSAGE AND ADMINISTRATION

Spray for smoothing hair and promoting hair growth

WARNINGS

keep out of children

INACTIVE INGREDIENT

AQUA

INDICATIONS AND USAGE

For daily hair care

keep out of children

PURPOSE

Smooth hair and promote hair growth